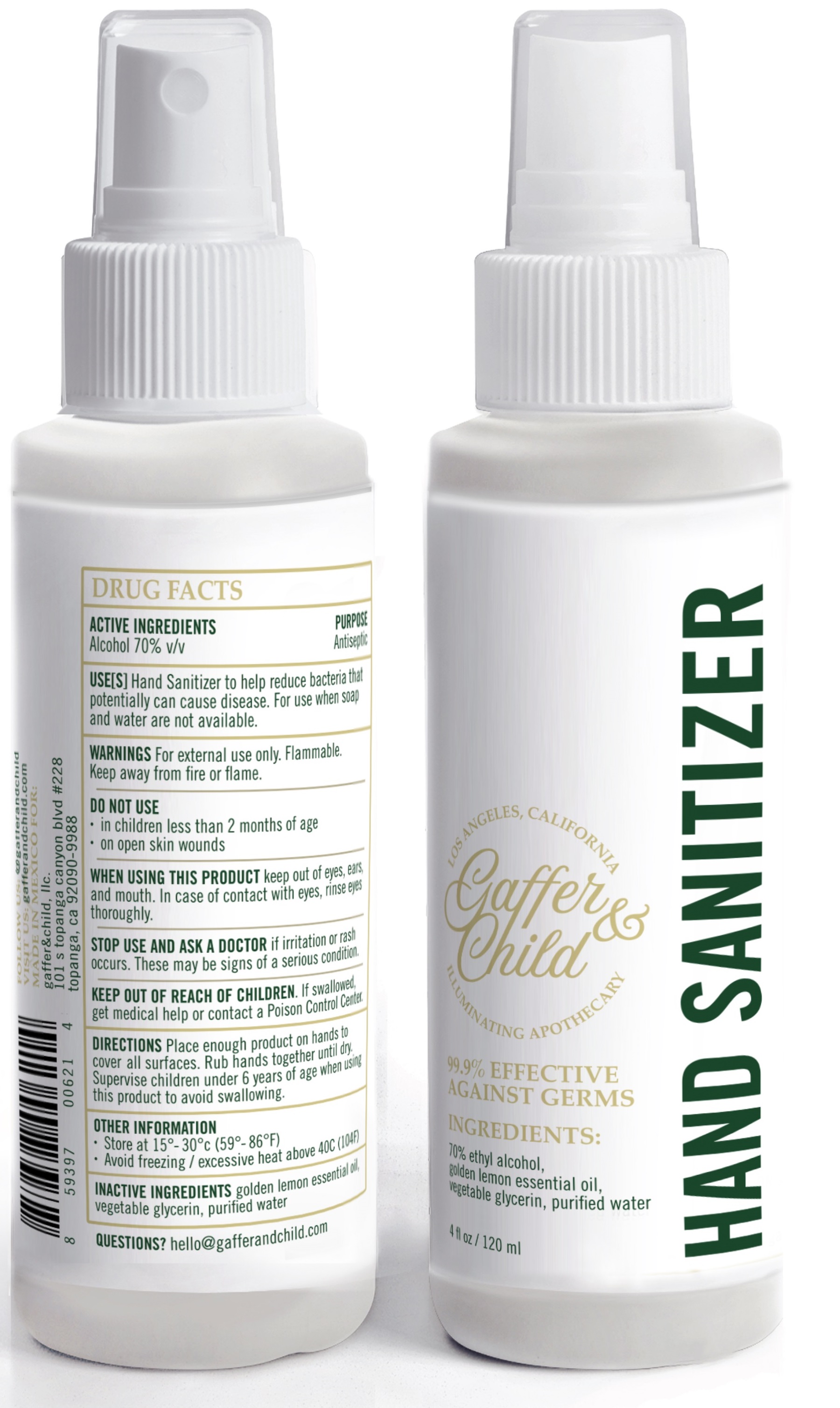 DRUG LABEL: Gaffer and Child Hand Sanitizer
NDC: 80634-001 | Form: SPRAY
Manufacturer: Gaffer and Child, LLC
Category: otc | Type: HUMAN OTC DRUG LABEL
Date: 20201008

ACTIVE INGREDIENTS: ALCOHOL 0.7 mL/1 mL
INACTIVE INGREDIENTS: GLYCERIN; WATER

Gaffer and Child Hand Sanitizer

ACTIVE INGREDIENTS

Alcohol 70% v/v

PURPOSE

Antiseptic

USE(S)

Hand Sanitizer to help reduce bacteria that potentially can cause disease. For use when soap and water are not available.

WARNINGS

For external use only. Flammable. Keep away from fire or flame.

DO NOT USE

- in children less than 2 months of age
- on open skin wounds

WHEN USING THIS PRODUCT

keep out of eyes, ears and mouth. In case of contact with eyes, rinse eyes thoroughly

STOP USE AND ASK A DOCTOR

if irritation or rash occurs. These may be signs of a serious condition.

KEEP OUT OF REACH OF CHILDREN.

If swallowed, get medical help or contact a Poison Control Center

DIRECTIONS

Place enough product on hands to cover all surfaces. Rub hands together until dry.
Supervise children under 6 years of age when using this product to avoid swallowing.

OTHER INFORMATION

- Store at 15°-30°C (59°-86°F)
- Avoid freezing and excessive heat above 40C (104F)

INACTIVE INGREDIENTS

golden lemon essential oil, vegetable glycerin, purified water

QUESTIONS?

hello@gafferandchild.com